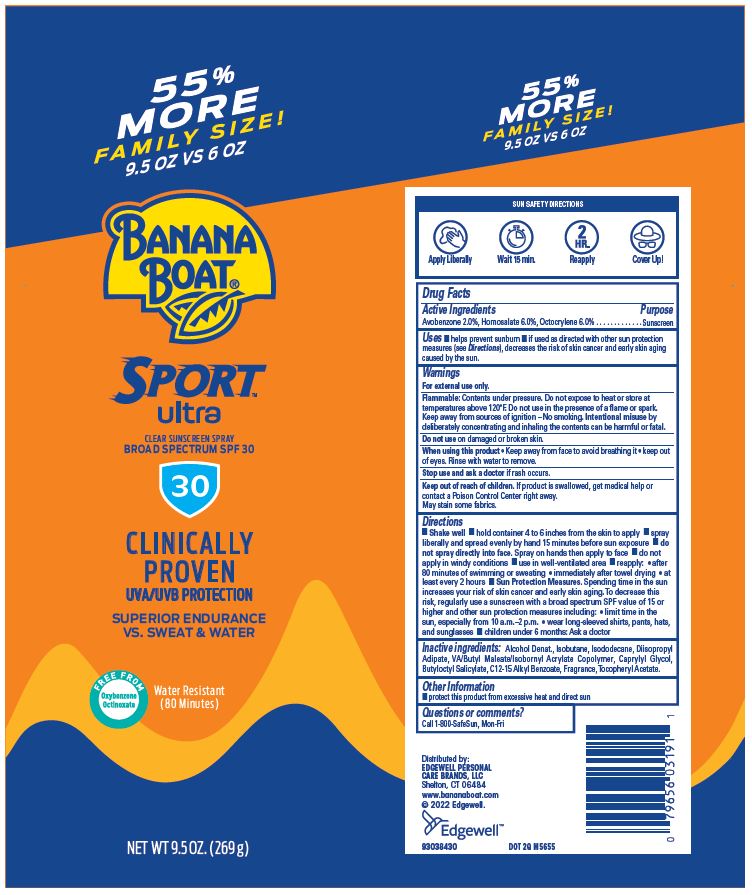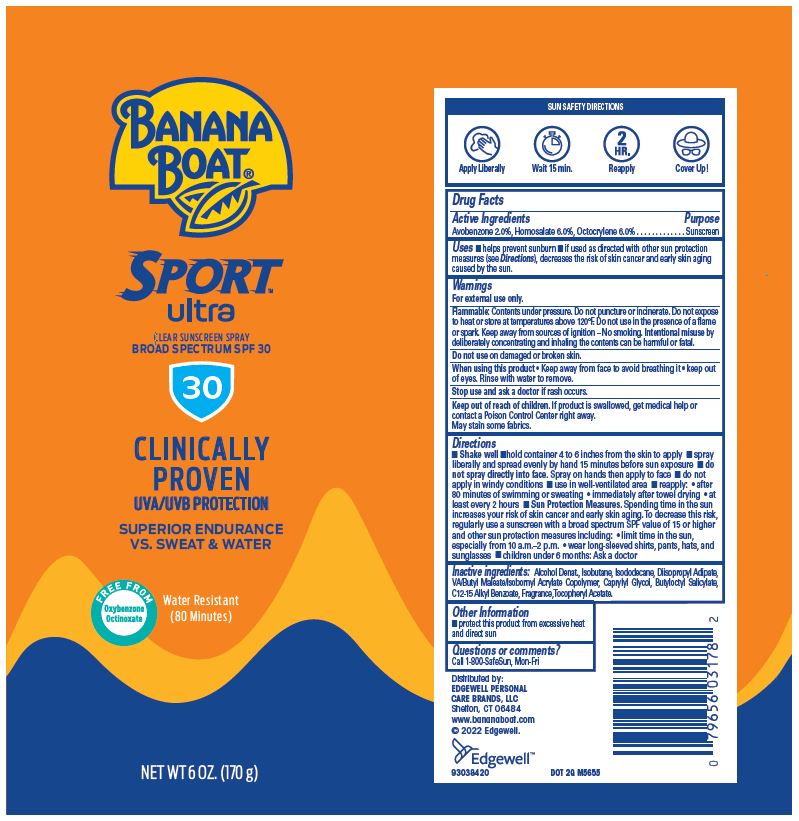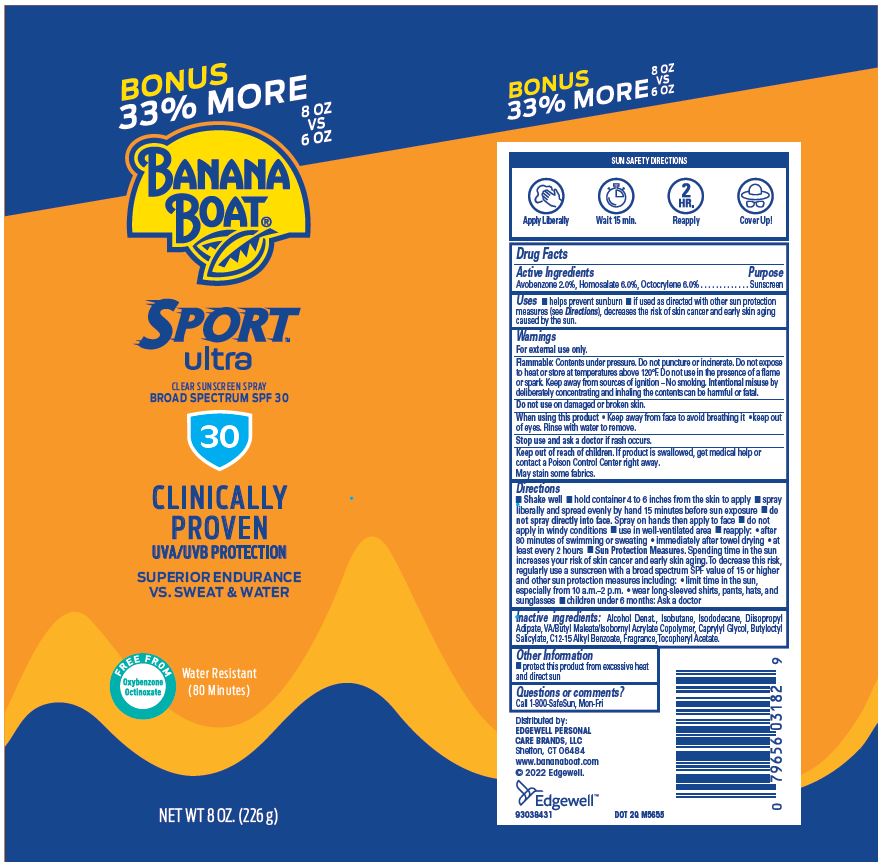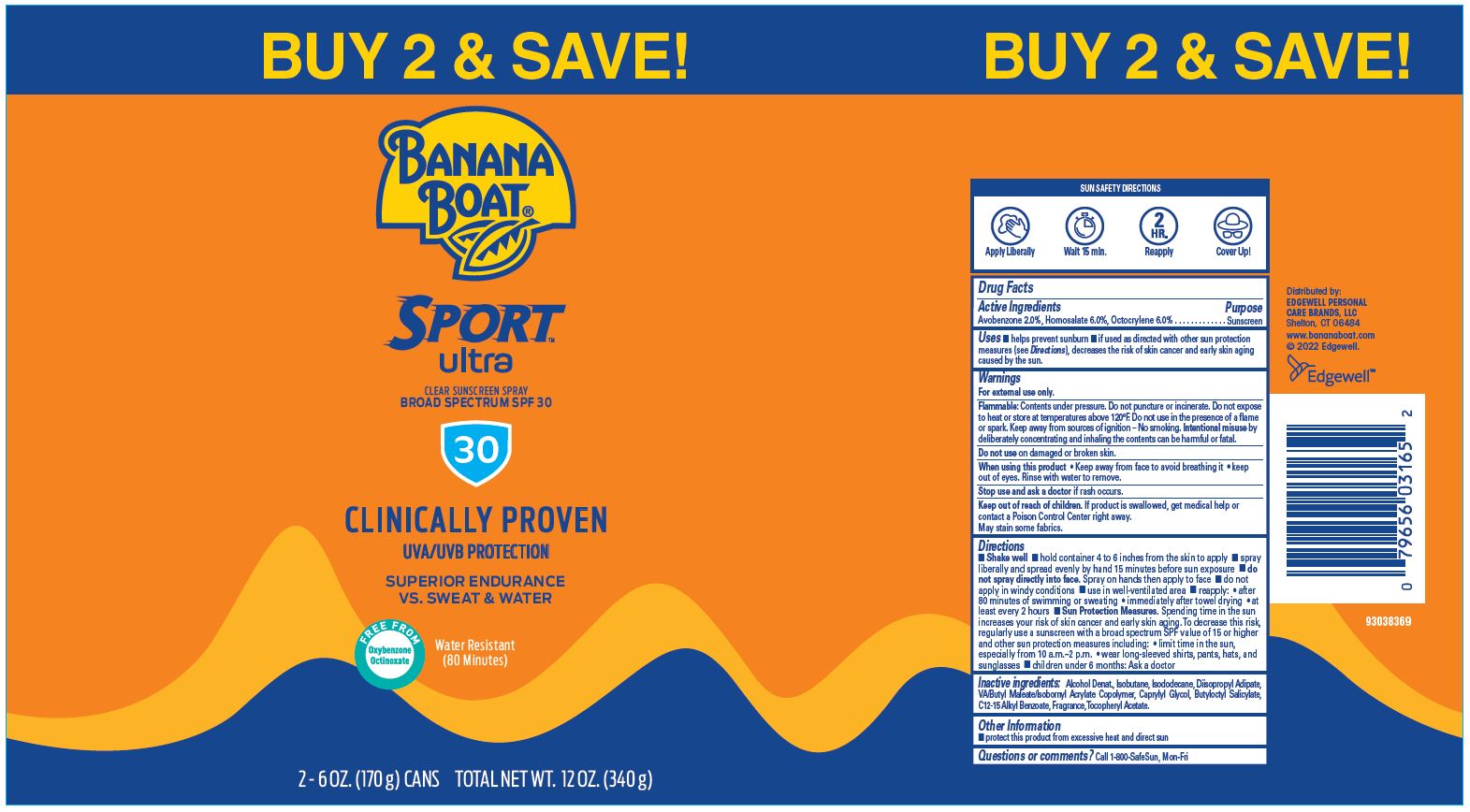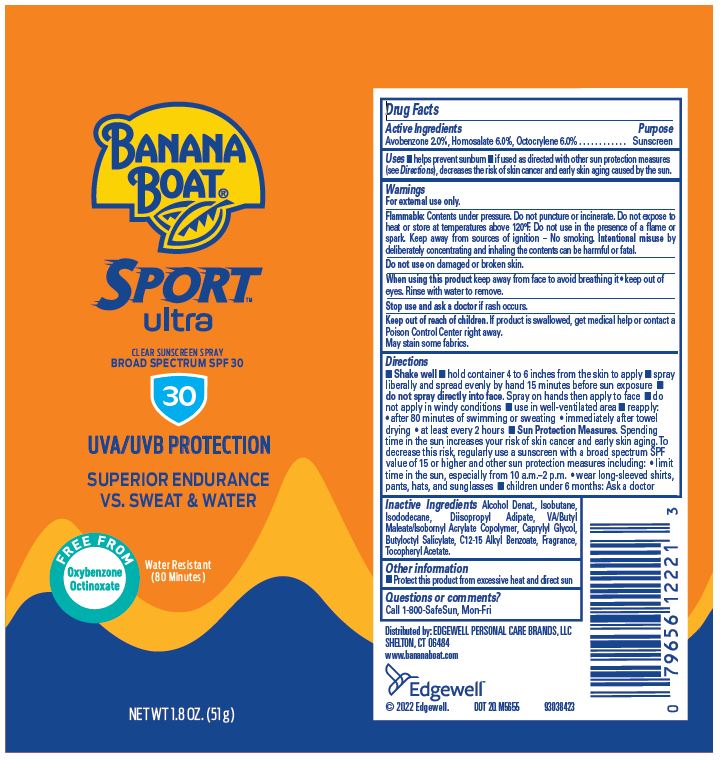 DRUG LABEL: Banana Boat
NDC: 63354-341 | Form: SPRAY
Manufacturer: Edgewell Personal Care Brands LLC
Category: otc | Type: HUMAN OTC DRUG LABEL
Date: 20251202

ACTIVE INGREDIENTS: AVOBENZONE 2 g/100 g; HOMOSALATE 6 g/100 g; OCTOCRYLENE 6 g/100 g
INACTIVE INGREDIENTS: BUTYLOCTYL SALICYLATE; ALCOHOL; ISOBUTANE; ALKYL (C12-15) BENZOATE; ISODODECANE; DIISOPROPYL ADIPATE; CAPRYLYL GLYCOL; .ALPHA.-TOCOPHEROL ACETATE

Active Ingredients

Avobenzone 2%, Homosalate 6%, Octocrylene 6%

Purpose

Sunscreen

Uses

Helps prevent sunburn.

If used as directed with other sun protection measures (see Directions), decreases the risk of skin cancer and early skin aging caused by the sun.

Warnings

For external use only.

Flammable: Contents under pressure. Do not expose to heat or store at temperatures above 120°F. Do not use in the presence of a flame or spark. Keep away from sources of ignition – No smoking. Intentional misuse by deliberately concentrating and inhaling the contents can be harmful or fatal.

May stain some fabrics.

Do not use

on damaged or broken skin.

When using this product

Keep away from face to avoid breathing it. Keep out of eyes. Rinse with water to remove.

Stop use and ask a doctor

if rash occurs.

Keep out of reach of children

If product is swallowed, get medical help or contact a Poison Control Center right away.

Directions

Shake well. • hold container 4 to 6 inches from the skin to apply • spray liberally and spread evenly by hand 15 minutes before sun exposure • do not spray directly into face. Spray on hands then apply to face. Do not apply in windy conditions • use in well-ventilated area • reapply: • after 80 minutes of swimming or sweating • immediately after towel drying • at least every 2 hours. Sun Protection Measures. Spending time in the sun increases your risk of skin cancer and early skin aging. To decrease this risk, regularly use a sunscreen with a broad spectrum SPF value of 15 or higher and other sun protection measures including: • limit time in the sun, especially from 10 a.m.–2 p.m. • wear long-sleeved shirts, pants, hats, and sunglasses • children under 6 months: Ask a doctor

Inactive Ingredients

Alcohol Denat., Isobutane, Isododecane, Diisopropyl Adipate, VA/Butyl Maleate/Isobornyl Acrylate Copolymer, Caprylyl Glycol, Butyloctyl Salicylate, C12-15 Alkyl Benzoate, Fragrance, Tocopheryl Acetate.

Other Information

protect this product from excessive heat and direct sun

Principal Display Panel

BANANA
BOAT®
SPORT
ultra
CLEAR SUNSCREEN SPRAY
BROAD SPECTRUM SPF 30
30
UVA/UVB PROTECTION
SUPERIOR ENDURANCE
VS. SWEAT & WATER
FREE FROM
Oxybenzone
Octinoxate
Water Resistant
(80 Minutes)
NET WT 1.8 OZ. (51 g)

BANANA
BOAT®
SPORT
ultra
CLEAR SUNSCREEN SPRAY
BROAD SPECTRUM SPF 30
30
CLINICALLY
PROVEN
UVA/UVB PROTECTION
SUPERIOR ENDURANCE
VS. SWEAT & WATER
FREE FROM
Oxybenzone
Octinoxate
Water Resistant
(80 Minutes)
NET WT 6 OZ. (170 g)

BONUS
33% MORE
8 OZ
VS
6 OZ
BANANA
BOAT®
SPORT
ultra
CLEAR SUNSCREEN SPRAY
BROAD SPECTRUM SPF 30
30
CLINICALLY
PROVEN
UVA/UVB PROTECTION
SUPERIOR ENDURANCE
VS. SWEAT & WATER
FREE FROM
Oxybenzone
Octinoxate
Water Resistant
(80 Minutes)
NET WT 8 OZ. (226 g)

55%
MORE
9.5 OZ VS 6 OZ
BANANA
BOAT®
SPORT
ultra
CLEAR SUNSCREEN SPRAY
BROAD SPECTRUM SPF 30
30
CLINICALLY
PROVEN
UVA/UVB PROTECTION
SUPERIOR ENDURANCE
VS. SWEAT & WATER
FREE FROM
Oxybenzone
Octinoxate
Water Resistant
(80 Minutes)
NET WT 9.5 OZ. (269 g)

BUY 2 & SAVE!
BANANA
BOAT®
SPORT
ultra
CLEAR SUNSCREEN SPRAY
BROAD SPECTRUM SPF 30
30
CLINICALLY PROVEN
UVA/UVB PROTECTION
SUPERIOR ENDURANCE
VS. SWEAT & WATER
FREE FROM
Oxybenzone
Octinoxate
Water Resistant
(80 Minutes)
2 - 6 OZ. (170 g) CANS TOTAL NET WT. 12 OZ. (340 g)